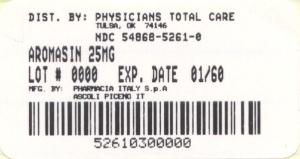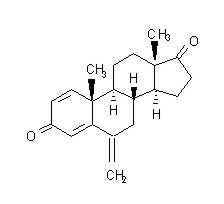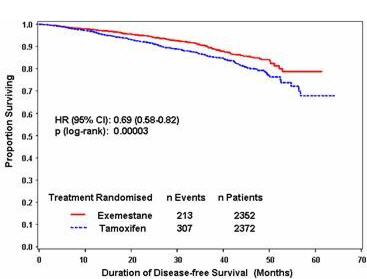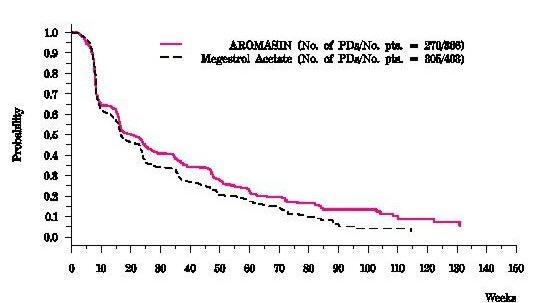 DRUG LABEL: Aromasin
NDC: 54868-5261 | Form: TABLET
Manufacturer: Physicians Total Care, Inc.
Category: prescription | Type: HUMAN PRESCRIPTION DRUG LABEL
Date: 20100104

ACTIVE INGREDIENTS: EXEMESTANE 25 mg/1 1
INACTIVE INGREDIENTS: MANNITOL; CROSPOVIDONE; POLYSORBATE 80; HYPROMELLOSE; SILICON DIOXIDE; CELLULOSE, MICROCRYSTALLINE; SODIUM STARCH GLYCOLATE TYPE A POTATO; MAGNESIUM STEARATE; POLYETHYLENE GLYCOL 6000; SUCROSE; MAGNESIUM CARBONATE; TITANIUM DIOXIDE; METHYLPARABEN; POLYVINYL ALCOHOL

DESCRIPTION

AROMASIN® Tablets for oral administration contain 25 mg of exemestane, an irreversible, steroidal aromatase inactivator. Exemestane is chemically described as 6-methylenandrosta-1,4-diene-3,17-dione. Its molecular formula is C20H24O2 and its structural formula is as follows:

The active ingredient is a white to slightly yellow crystalline powder with a molecular weight of 296.41. Exemestane is freely soluble in N, N-dimethylformamide, soluble in methanol, and practically insoluble in water.

Each AROMASIN Tablet contains the following inactive ingredients: mannitol, crospovidone, polysorbate 80, hypromellose, colloidal silicon dioxide, microcrystalline cellulose, sodium starch glycolate, magnesium stearate, simethicone, polyethylene glycol 6000, sucrose, magnesium carbonate, titanium dioxide, methylparaben, and polyvinyl alcohol.

CLINICAL PHARMACOLOGY

Mechanism of Action

Breast cancer cell growth may be estrogen-dependent. Aromatase is the principal enzyme that converts androgens to estrogens both in pre- and postmenopausal women. While the main source of estrogen (primarily estradiol) is the ovary in premenopausal women, the principal source of circulating estrogens in postmenopausal women is from conversion of adrenal and ovarian androgens (androstenedione and testosterone) to estrogens (estrone and estradiol) by the aromatase enzyme in peripheral tissues. Estrogen deprivation through aromatase inhibition is an effective and selective treatment for some postmenopausal patients with hormone-dependent breast cancer.

Exemestane is an irreversible, steroidal aromatase inactivator, structurally related to the natural substrate androstenedione. It acts as a false substrate for the aromatase enzyme, and is processed to an intermediate that binds irreversibly to the active site of the enzyme causing its inactivation, an effect also known as "suicide inhibition." Exemestane significantly lowers circulating estrogen concentrations in postmenopausal women, but has no detectable effect on adrenal biosynthesis of corticosteroids or aldosterone. Exemestane has no effect on other enzymes involved in the steroidogenic pathway up to a concentration at least 600 times higher than that inhibiting the aromatase enzyme.

Pharmacokinetics

Following oral administration to healthy postmenopausal women, exemestane is rapidly absorbed. After maximum plasma concentration is reached, levels decline polyexponentially with a mean terminal half-life of about 24 hours. Exemestane is extensively distributed and is cleared from the systemic circulation primarily by metabolism. The pharmacokinetics of exemestane are dose proportional after single (10 to 200 mg) or repeated oral doses (0.5 to 50 mg). Following repeated daily doses of exemestane 25 mg, plasma concentrations of unchanged drug are similar to levels measured after a single dose.

Pharmacokinetic parameters in postmenopausal women with advanced breast cancer following single or repeated doses have been compared with those in healthy, postmenopausal women. Exemestane appeared to be more rapidly absorbed in the women with breast cancer than in the healthy women, with a mean tmax of 1.2 hours in the women with breast cancer and 2.9 hours in the healthy women. After repeated dosing, the average oral clearance in women with advanced breast cancer was 45% lower than the oral clearance in healthy postmenopausal women, with corresponding higher systemic exposure. Mean AUC values following repeated doses in women with breast cancer (75.4 ng∙h/mL) were about twice those in healthy women (41.4 ng∙h/mL).

Absorption

Following oral administration of radiolabeled exemestane, at least 42% of radioactivity was absorbed from the gastrointestinal tract. Exemestane plasma levels increased by approximately 40% after a high-fat breakfast.

Distribution

Exemestane is distributed extensively into tissues. Exemestane is 90% bound to plasma proteins and the fraction bound is independent of the total concentration. Albumin and α1-acid glycoprotein both contribute to the binding. The distribution of exemestane and its metabolites into blood cells is negligible.

Metabolism and Excretion

Following administration of radiolabeled exemestane to healthy postmenopausal women, the cumulative amounts of radioactivity excreted in urine and feces were similar (42 ± 3% in urine and 42 ± 6% in feces over a 1-week collection period). The amount of drug excreted unchanged in urine was less than 1% of the dose. Exemestane is extensively metabolized, with levels of the unchanged drug in plasma accounting for less than 10% of the total radioactivity. The initial steps in the metabolism of exemestane are oxidation of the methylene group in position 6 and reduction of the 17-keto group with subsequent formation of many secondary metabolites. Each metabolite accounts only for a limited amount of drug-related material. The metabolites are inactive or inhibit aromatase with decreased potency compared with the parent drug. One metabolite may have androgenic activity (see Pharmacodynamics, Other Endocrine Effects). Studies using human liver preparations indicate that cytochrome P-450 3A4 (CYP 3A4) is the principal isoenzyme involved in the oxidation of exemestane.

Special Populations Geriatric

Healthy postmenopausal women aged 43 to 68 years were studied in the pharmacokinetic trials. Age-related alterations in exemestane pharmacokinetics were not seen over this age range.

Gender

The pharmacokinetics of exemestane following administration of a single, 25-mg tablet to fasted healthy males (mean age 32 years) were similar to the pharmacokinetics of exemestane in fasted healthy postmenopausal women (mean age 55 years).

Race

The influence of race on exemestane pharmacokinetics has not been evaluated.

Hepatic Insufficiency

The pharmacokinetics of exemestane have been investigated in subjects with moderate or severe hepatic insufficiency (Childs-Pugh B or C). Following a single 25-mg oral dose, the AUC of exemestane was approximately 3 times higher than that observed in healthy volunteers (see PRECAUTIONS).

Renal Insufficiency

The AUC of exemestane after a single 25-mg dose was approximately 3 times higher in subjects with moderate or severe renal insufficiency (creatinine clearance less than 35 mL/min/1.73 m^2) compared with the AUC in healthy volunteers (see PRECAUTIONS).

Pediatric

The pharmacokinetics of exemestane have not been studied in pediatric patients.

Drug-Drug Interactions

Exemestane is metabolized by cytochrome P-450 3A4 (CYP 3A4) and aldoketoreductases. It does not inhibit any of the major CYP isoenzymes, including CYP 1A2, 2C9, 2D6, 2E1, and 3A4. In a clinical pharmacokinetic study, ketoconazole showed no significant influence on the pharmacokinetics of exemestane. Although no other formal drug-drug interaction studies have been conducted, significant effects on exemestane clearance by CYP isoenzymes inhibitors appear unlikely. In a pharmacokinetic interaction study of 10 healthy postmenopausal volunteers pretreated with potent CYP 3A4 inducer rifampicin 600 mg daily for 14 days followed by a single dose of exemestane 25 mg, the mean plasma Cmax and AUC 0–∞ of exemestane were decreased by 41% and 54%, respectively (see PRECAUTIONS and DOSAGE AND ADMINISTRATION).

Pharmacodynamics Effect on Estrogens

Multiple doses of exemestane ranging from 0.5 to 600 mg/day were administered to postmenopausal women with advanced breast cancer. Plasma estrogen (estradiol, estrone, and estrone sulfate) suppression was seen starting at a 5-mg daily dose of exemestane, with a maximum suppression of at least 85% to 95% achieved at a 25-mg dose. Exemestane 25 mg daily reduced whole body aromatization (as measured by injecting radiolabeled androstenedione) by 98% in postmenopausal women with breast cancer. After a single dose of exemestane 25 mg, the maximal suppression of circulating estrogens occurred 2 to 3 days after dosing and persisted for 4 to 5 days.

Effect on Corticosteroids

In multiple-dose trials of doses up to 200 mg daily, exemestane selectivity was assessed by examining its effect on adrenal steroids. Exemestane did not affect cortisol or aldosterone secretion at baseline or in response to ACTH at any dose. Thus, no glucocorticoid or mineralocorticoid replacement therapy is necessary with exemestane treatment.

Other Endocrine Effects

Exemestane does not bind significantly to steroidal receptors, except for a slight affinity for the androgen receptor (0.28% relative to dihydrotestosterone). The binding affinity of its 17-dihydrometabolite for the androgen receptor, however, is 100-times that of the parent compound. Daily doses of exemestane up to 25 mg had no significant effect on circulating levels of androstenedione, dehydroepiandrosterone sulfate, or 17-hydroxyprogesterone, and were associated with small decreases in circulating levels of testosterone. Increases in testosterone and androstenedione levels have been observed at daily doses of 200 mg or more. A dose-dependent decrease in sex hormone binding globulin (SHBG) has been observed with daily exemestane doses of 2.5 mg or higher. Slight, nondose-dependent increases in serum luteinizing hormone (LH) and follicle-stimulating hormone (FSH) levels have been observed even at low doses as a consequence of feedback at the pituitary level. Exemestane 25 mg daily had no significant effect on thyroid function [free triiodothyronine (FT3), free thyroxine (FT4) and thyroid stimulating hormone (TSH)].

Coagulation and Lipid Effects

In study 027 of postmenopausal women with early breast cancer treated with exemestane (N=73) or placebo (N=73), there was no change in the coagulation parameters activated partial thromboplastin time [APTT], prothrombin time [PT] and fibrinogen. Plasma HDL cholesterol was decreased 6–9% in exemestane treated patients; total cholesterol, LDL cholesterol, triglycerides, apolipoprotein-A1, apolipoprotein-B, and lipoprotein-a were unchanged. An 18% increase in homocysteine levels was also observed in exemestane treated patients compared with a 12% increase seen with placebo.

CLINICAL STUDIES

Adjuvant Treatment in Early Breast Cancer

The Intergroup Exemestane Study 031 (IES) was a randomized, double-blind, multicenter, multinational study comparing exemestane (25 mg/day) versus tamoxifen (20 or 30 mg/day) in postmenopausal women with early breast cancer. Patients who remained disease-free after receiving adjuvant tamoxifen therapy for 2 to 3 years were randomized to receive 3 to 2 years of AROMASIN or tamoxifen to complete a total of 5 years of hormonal therapy.

The primary objective of the study was to determine whether, in terms of disease-free survival, it was more effective to switch to AROMASIN rather than continuing tamoxifen therapy for the remainder of five years. Disease-free survival was defined as the time from randomization to time of local or distant recurrence of breast cancer, contralateral invasive breast cancer, or death from any cause.

The secondary objectives were to compare the two regimens in terms of overall survival and long-term tolerability. Time to contralateral invasive breast cancer and distant recurrence-free survival were also evaluated.

A total of 4724 patients in the intent-to-treat (ITT) analysis were randomized to AROMASIN (exemestane tablets) 25 mg once daily (N = 2352) or to continue to receive tamoxifen once daily at the same dose received before randomization (N = 2372). Demographics and baseline tumor characteristics are presented in Table 1. Prior breast cancer therapy is summarized in Table 2.

Table 1. Demographic and Baseline Tumor Characteristics from the IES Study of Postmenopausal Women with Early Breast Cancer (ITT Population)
Parameter | Exemestane | Tamoxifen
Age (years): | (N = 2352) | (N = 2372)
Median age (range) | 63.0 (38.0 - 96.0) | 63.0 (31.0 - 90.0)
Race, n (%):
Caucasian | 2315 (98.4) | 2333 (98.4)
Hispanic | 13 (0.6) | 13 (0.5)
Asian | 10 (0.4) | 9 (0.4)
Black | 7 (0.3) | 10 (0.4)
Other/not reported | 7 (0.3) | 7 (0.3)
Nodal status, n (%):
Negative | 1217 (51.7) | 1228 (51.8)
Positive | 1051 (44.7) | 1044 (44.0)
1-3 Positive nodes | 721 (30.7) | 708 (29.8)
4-9 Positive nodes | 239 (10.2) | 244 (10.3)
Greater than 9 Positive nodes | 88 (3.7) | 86 (3.6)
Not reported | 3 (0.1) | 6 (0.3)
Unknown or missing | 84 (3.6) | 100 (4.2)
Histologic type, n (%):
Infiltrating ductal | 1777 (75.6) | 1830 (77.2)
Infiltrating lobular | 341 (14.5) | 321 (13.5)
Other | 231 (9.8) | 213 (9.0)
Unknown or missing | 3 (0.1) | 8 (0.3)
Receptor status (*), n (%):
ER and PgR Positive | 1331 (56.6) | 1319 (55.6)
ER Positive and PgR Negative/Unknown | 677 (28.8) | 692 (29.2)
ER Unknown and PgR Positive (**)/Unknown | 288 (12.2) | 291 (12.3)
ER Negative and PgR Positive | 6 (0.3) | 7 (0.3)
ER Negative and PgR Negative/Unknown (none positive) | 48 (2.0) | 58 (2.4)
Missing | 2 (0.1) | 5 (0.2)
Tumor Size, n (%):
Less than or equal to 0.5 cm | 58 (2.5) | 46 (1.9)
Greater than 0.5 - 1.0 cm | 315 (13.4) | 302 (12.7)
Greater than 1.0 - 2 cm | 1031 (43.8) | 1033 (43.5)
Greater than 2.0 - 5.0 cm | 833 (35.4) | 883 (37.2)
Greater than 5.0 cm | 62 (2.6) | 59 (2.5)
Not reported | 53 (2.3) | 49 (2.1)
Tumor Grade, n (%):
G1 | 397 (16.9) | 393 (16.6)
G2 | 977 (41.5) | 1007 (42.5)
G3 | 454 (19.3) | 428 (18.0)
G4 Unknown/Not Assessed/Not reported | 23 (1.0 501 (21.3) | 19 (0.8) 525 (22.1)

(*) Results for receptor status include the results of the post-randomization testing of specimens from subjects for whom receptor status was unknown at randomization.
(**) Only one subject in the exemestane group had unknown ER status and positive PgR status.

Table 2. Prior Breast Cancer Therapy of Patients in the IES Study of Postmenopausal Women with Early Breast Cancer (ITT Population)
Parameter | Exemestane (N = 2352) | Tamoxifen (N = 2372)
Type of surgery, n (%):
Mastectomy | 1232 (52.4) | 1242 (52.4)
Breast-conserving | 1116 (47.4) | 1123 (47.3)
Unknown or missing | 4 (0.2) | 7 (0.3)
Radiotherapy to the breast, n (%):
Yes | 1524 (64.8) | 1523 (64.2)
No | 824 (35.5) | 843 (35.5)
Not reported | 4 (0.2) | 6 (0.3)
Prior therapy, n (%):
Chemotherapy | 774 (32.9) | 769 (32.4)
Hormone replacement therapy | 567 (24.1) | 561 (23.7)
Bisphosphonates | 43 (1.8) | 34 (1.4)
Duration of tamoxifen therapy at randomization
months:
Median (range) | 28.5 (15.8 - 52.2) | 28.4 (15.6 - 63.0)
Tamoxifen dose, n (%):
20 mg | 2270 (96.5) | 2287 (96.4)
30 mg (*) | 78 (3.3) | 75 (3.2)
Not reported | 4 (0.2) | 10 (0.4)

(*) The 30 mg dose was used only in Denmark, where this dose was the standard of care.
After a median duration of therapy of 27 months and with a median follow-up of 34.5 months, 520 events were reported, 213 in the AROMASIN group and 307 in the tamoxifen group (Table 3).

Table 3. Primary Endpoint Events (ITT Population)
Event |  | First Event N (%)
 | Exemestane (N = 2352) |  | Tamoxifen (N = 2372)
Loco-regional recurrence | 34 (1.4) |  | 45 (1.90)
Distant recurrence | 126 (5.36) |  | 183 (7.72)
Second primary - contralateral breast cancer | 7 (0.30) |  | 25 (1.05)
Death - breast cancer | 1 (0.04 |  | 6 (0.25)
Death - other reason | 41 (1.74) |  | 43 (1.81)
Death - missing/unknown | 3 (0.13) |  | 5 (0.21)
Ipsilateral breast cancer | 1 (0.04) |  | 0
Total number of events | 213 (9.06) |  | 307 (12.94)

Disease-free survival in the intent-to-treat population was statistically significantly improved [Hazard Ratio (HR) = 0.69, 95% CI: 0.58, 0.82, P = 0.00003, Table 4, Figure 1] in the AROMASIN arm compared to the tamoxifen arm. In the hormone receptor-positive subpopulation representing about 85% of the trial patients, disease-free survival was also statistically significantly improved (HR = 0.65, 95% CI: 0.53, 0.79, P = 0.00001) in the AROMASIN arm compared to the tamoxifen arm. Consistent results were observed in the subgroups of patients with node negative or positive disease, and patients who had or had not received prior chemotherapy. Overall survival was not significantly different in the two groups, with 116 deaths occurring in the AROMASIN group and 137 in the tamoxifen group.

Table 4. Efficacy Results from the IES Study in Postmenopausal Women with Early Breast Cancer
 | Hazard Ratio | p-value
ITT Population | (95% CI) | (log-rank test)
Disease free survival | 0.69 (0.58 - 0.82) | 0.00003
Time to contralateral breast cancer | 0.32 (0.15 - 0.72) | 0.00340
Distant recurrence free survival | 0.74 (0.62 - 0.90) | 0.00207
Overall survival | 0.86 (0.67 - 1.10) | 0.22962
ER and/or PgR positive
Disease free survival | 0.65 (0.53 - 0.79) | 0.00001
Time to contralateral breast cancer | 0.22 (0.08 - 0.57) | 0.00069
Distant recurrence free survival | 0.73 (0.59 - 0.90) | 0.00367
Overall survival | 0.88 (0.67 - 1.17) | 0.37460

Figure 1. Disease Free Survival in the IES Study of Postmenopausal Women with Early Breast Cancer (ITT Population)

Treatment of Advanced Breast Cancer

Exemestane 25 mg administered once daily was evaluated in a randomized double-blind, multicenter, multinational comparative study and in two multicenter single-arm studies of postmenopausal women with advanced breast cancer who had disease progression after treatment with tamoxifen for metastatic disease or as adjuvant therapy. Some patients also have received prior cytotoxic therapy, either as adjuvant treatment or for metastatic disease.

The primary purpose of the three studies was evaluation of objective response rate (complete response [CR] and partial response [PR]). Time to tumor progression and overall survival were also assessed in the comparative trial. Response rates were assessed based on World Health Organization (WHO) criteria, and in the comparative study, were submitted to an external review committee that was blinded to patient treatment. In the comparative study, 769 patients were randomized to receive AROMASIN (exemestane tablets) 25 mg once daily (N = 366) or megestrol acetate 40 mg four times daily (N = 403). Demographics and baseline characteristics are presented in Table 5.

Table 5. Demographics and Baseline Characteristics from the Comparative Study of Postmenopausal Women with Advanced Breast Cancer Whose Disease Had Progressed after Tamoxifen Therapy
Parameter | AROMASIN (N = 366) | Megestrol Acetate (N = 403)
Median Age (range) | 65 (35-89) | 65 (30-91)
ECOG Performance Status 0 1 2 | 167 (46%) 162 (44%) 34 (9%) | 187 (46%) 172 (43%) 42 (10%)
Receptor Status ER and/or PgR + ER and PgR unknown Responders to prior tamoxifen NE for response to prior tamoxifen | 246 (67%) 116 (32%) 68 (19%) 46 (13%) | 274 (68%) 128 (32%) 85 (21%) 41 (10%)
Site of Metastasis Visceral + other sites Bone only Soft tissue only Bone & soft tissue | 207 (57%) 61 (17%) 54 (15%) 43 (12%) | 239 (59%) 73 (18%) 51 (13%) 38 (9%)
Measureable Disease | 287 (78%) | 314 (78%)
Prior Tamoxifen Therapy Adjuvant or Neoadjuvant Advanced Disease, Outcome CR, PR or SD greater than or equal to 6 months SD less than months, PD or NE | 145 (40%) 179 (49%) 42 (12%) | 152 (38%) 210 (52%) 41 (10%)
Prior Chemotherapy For advanced disease + adjuvant Adjuvant only No chemotherapy | 58 (16%) 104 (28%) 203 (56%) | 67 (17%) 108 (27%) 226 (56%)

The efficacy results from the comparative study are shown in Table 6. The objective response rates observed in the two treatment arms showed that AROMASIN was not different from megestrol acetate. Response rates for AROMASIN from the two single-arm trials were 23.4% and 28.1%.

Table 6. Efficacy Results from the Comparative Study of Postmenopausal Women with Advanced Breast Cancer Whose Disease Had Progressed after Tamoxifen Therapy
Response Characteristics | AROMASIN (N =366) |  | Megestrol Acetate (N=403)
Objective Response Rate = CR + PR (%) | 15.0 |  | 12.4
Difference in Response Rate (AR-MA) 95% C.I. |  | 2.6 7.5, -2.3
CR (%) | 2.2 |  | 1.2
PR (%) | 12.8 |  | 11.2
SD > 24 Weeks (%) | 21.3 |  | 21.1
Median Duration of Response (weeks) | 76.1 |  | 71.0
Median TTP (weeks) Hazard Ratio (AR-MA) | 20.3 | 0.84 | 16.6

Abbreviations: CR = complete response, PR = partial response, SD = stable disease (no change), TTP = time to tumor progression, C.I. = confidence interval, MA = megestrol acetate, AR = AROMASIN

There were too few deaths occurring across treatment groups to draw conclusions on overall survival differences. The Kaplan-Meier curve for time to tumor progression in the comparative study is shown in Figure 2.

Figure 2. Time to Tumor Progression in the Comparative Study of Postmenopausal Women With Advanced Breast Cancer Whose Disease Had Progressed After Tamoxifen Therapy

INDICATIONS AND USAGE

AROMASIN is indicated for adjuvant treatment of postmenopausal women with estrogen-receptor positive early breast cancer who have received two to three years of tamoxifen and are switched to AROMASIN for completion of a total of five consecutive years of adjuvant hormonal therapy.

AROMASIN is indicated for the treatment of advanced breast cancer in postmenopausal women whose disease has progressed following tamoxifen therapy.

CONTRAINDICATIONS

AROMASIN Tablets are contraindicated in patients with a known hypersensitivity to the drug or to any of the excipients.

WARNINGS

AROMASIN Tablets may cause fetal harm when administered to a pregnant woman. Radioactivity related to ^14C-exemestane crossed the placenta of rats following oral administration of 1 mg/kg exemestane. The concentration of exemestane and its metabolites was approximately equivalent in maternal and fetal blood. When rats were administered exemestane from 14 days prior to mating until either days 15 or 20 of gestation, and resuming for the 21 days of lactation, an increase in placental weight was seen at 4 mg/kg/day (approximately 1.5 times the recommended human daily dose on a mg/m^2 basis). Prolonged gestation and abnormal or difficult labor was observed at doses equal to or greater than 20 mg/kg/day. Increased resorption, reduced number of live fetuses, decreased fetal weight, and retarded ossification were also observed at these doses. No malformations were noted when exemestane was administered to pregnant rats during the organogenesis period at doses up to 810 mg/kg/day (approximately 320 times the recommended human dose on a mg/m^2 basis). Daily doses of exemestane, given to rabbits during organogenesis caused a decrease in placental weight at 90 mg/kg/day (approximately 70 times the recommended human daily dose on a mg/m^2 basis). Abortions, an increase in resorptions, and a reduction in fetal body weight were seen at 270 mg/kg/day. There was no increase in the incidence of malformations in rabbits at doses up to 270 mg/kg/day (approximately 210 times the recommended human dose on a mg/m^2 basis).

There are no studies in pregnant women using AROMASIN. AROMASIN is indicated for postmenopausal women. If there is exposure to AROMASIN during pregnancy, the patient should be apprised of the potential hazard to the fetus and potential risk for loss of the pregnancy.

PRECAUTIONS

General

AROMASIN Tablets should not be administered to premenopausal women. AROMASIN should not be coadministered with estrogen-containing agents as these could interfere with its pharmacologic action.

Hepatic Insufficiency

The pharmacokinetics of exemestane have been investigated in subjects with moderate or severe hepatic insufficiency (Childs-Pugh B or C). Following a single 25-mg oral dose, the AUC of exemestane was approximately 3 times higher than that observed in healthy volunteers. The safety of chronic dosing in patients with moderate or severe hepatic impairment has not been studied. Based on experience with exemestane at repeated doses up to 200 mg daily that demonstrated a moderate increase in non-life threatening adverse events, dosage adjustment does not appear to be necessary.

Renal Insufficiency

The AUC of exemestane after a single 25-mg dose was approximately 3 times higher in subjects with moderate or severe renal insufficiency (creatinine clearance less than 35 mL/min/1.73 m^2) compared with the AUC in healthy volunteers. The safety of chronic dosing in patients with moderate or severe renal impairment has not been studied. Based on experience with exemestane at repeated doses up to 200 mg daily that demonstrated a moderate increase in non-life threatening adverse events, dosage adjustment does not appear to be necessary.

Laboratory Tests

In patients with early breast cancer the incidence of hematological abnormalities of Common Toxicity Criteria (CTC) grade greater than or equal to 1 was lower in the exemestane treatment group, compared with tamoxifen. Incidence of CTC grade 3 or 4 abnormalities was low (approximately 0.1%) in both treatment groups. Approximately 20% of patients receiving exemestane in clinical studies in advanced breast cancer, experienced CTC grade 3 or 4 lymphocytopenia. Of these patients, 89% had a pre-existing lower grade lymphopenia. Forty percent of patients either recovered or improved to a lesser severity while on treatment. Patients did not have a significant increase in viral infections, and no opportunistic infections were observed. Elevations of serum levels of AST, ALT, alkaline phosphatase and gamma glutamyl transferase less than greater than 5 times the upper value of the normal range (i.e., greater than or equal to CTC grade 3) have been rarely reported in patients treated for advanced breast cancer but appear mostly attributable to the underlying presence of liver and/or bone metastases. In the comparative study in advanced breast cancer patients, CTC grade 3 or 4 elevation of gamma glutamyl transferase without documented evidence of liver metastasis was reported in 2.7% of patients treated with AROMASIN and in 1.8% of patients treated with megestrol acetate.

In patients with early breast cancer, elevations in bilirubin, alkaline phosphatase, and creatinine were more common in those receiving exemestane than either tamoxifen or placebo. Treatment emergent bilirubin elevations (any CTC grade) occurred in 5.3% of exemestane patients and 0.8% of tamoxifen patients on the IES, and in 6.9% of exemestane treated patients vs. 0% of placebo treated patients on the 027 study. CTC grade 3–4 increases in bilirubin occurred in 0.9% of exemestane treated patients compared to 0.1% of tamoxifen treated patients. Alkaline phosphatase elevations of any CTC grade occurred in 15.0% of exemestane treated patients on the IES compared to 2.6% of tamoxifen treated patients, and in 13.7% of exemestane treated patients compared to 6.9% of placebo treated patients on study 027. Creatinine elevations occurred in 5.8% of exemestane treated patients and 4.3% of tamoxifen treated patients on the IES and in 5.5% of exemestane treated patients and 0% of placebo treated patients on study 027.

Reductions in bone mineral density (BMD) over time are seen with exemestane use. Table 7 describes changes in BMD from baseline to 24 months in patients receiving exemestane compared to patients receiving tamoxifen (IES) or placebo (027). Concomitant use of bisphosphonates, Vitamin D supplementation and Calcium was not allowed.

Table 7: Percent Change in BMD from Baseline to 24 months, Exemestane vs. Control*
 | IES | IES | 027 | 027
BMD | Exemestane N=29 | Tamoxifen N=38 | Exemestane N=59 | Placebo N=65
Lumbar spine (%) | -3.14 | -0.18 | -3.51 | -2.35
Femoral neck (%) | -4.15 | -0.33 | -4.57 | -2.59

* For patients who had 24-month data.
Drug Interactions

Exemestane is extensively metabolized by CYP 3A4, but coadministration of ketoconazole, a potent inhibitor of CYP 3A4, has no significant effect on exemestane pharmacokinetics. Significant pharmacokinetic interactions mediated by inhibition of CYP isoenzymes therefore appear unlikely. Co-medications that induce CYP 3A4 (e.g., rifampicin, phenytoin, carbamazepine, phenobarbital, or St. John's wort) may significantly decrease exposure to exemestane. Dose modification is recommended for patients who are also receiving a potent CYP 3A4 inducer (see DOSAGE AND ADMINISTRATION and CLINICAL PHARMACOLOGY).

Drug/Laboratory Tests Interactions

No clinically relevant changes in the results of clinical laboratory tests have been observed.

Carcinogenesis, Mutagenesis, Impairment of Fertility

A 2-year carcinogenicity study in mice at doses of 50, 150 and 450 mg/kg/day exemestane (gavage), resulted in an increased incidence of hepatocellular adenomas and/or carcinomas in both genders at the high dose level. Plasma AUCs(0–24hr) at the high dose were 2575 ± 386 and 5667 ± 1833 ng.hr/mL in males and females (approx. 34 and 75 fold the AUC in postmenopausal patients at the recommended clinical dose). An increased incidence of renal tubular adenomas was observed in male mice at the high dose of 450 mg/kg/day. Since the doses tested in mice did not achieve an MTD, neoplastic findings in organs other than liver and kidneys remain unknown.

A separate carcinogenicity study was conducted in rats at the doses of 30, 100 and 315 mg/kg/day exemestane (gavage) for 92 weeks in males and 2 years in females. No evidence of carcinogenic activity up to the highest dose tested of 315 mg/kg/day was observed in females. The male rat study was inconclusive since it was terminated prematurely at Week 92. At the highest dose, plasma AUC(0–24hr) levels in male (1418 ± 287 ng.hr/mL) and female (2318 ± 1067 ng.hr/mL) rats were 19 and 31 fold higher than those measured in postmenopausal cancer patients, receiving the recommended clinical dose.

Exemestane was not mutagenic in vitro in bacteria (Ames test) or mammalian cells (V79 Chinese hamster lung cells). Exemestane was clastogenic in human lymphocytes in vitro without metabolic activation but was not clastogenic in vivo (micronucleus assay in mouse bone marrow). Exemestane did not increase unscheduled DNA synthesis in rat hepatocytes when tested in vitro.

In a pilot reproductive study in rats, male rats were treated with doses of 125–1000 mg/kg/day exemestane, beginning 63 days prior to and during cohabitation. Untreated female rats showed reduced fertility when mated to males treated with greater than or equal to 500 mg/kg/day exemestane (greater than or equal to 200 times the recommended human dose on a mg/m^2 basis). In a separate study, exemestane was given to female rats at 4–100 mg/kg/day beginning 14 days prior to mating and through day 15 or 20 of gestation. Exemestane increased the placental weights at greater than or equal to 4 mg/kg/day greater than or equal to 1.5 times the human dose on a mg/m^2 basis). Exemestane showed no effects on ovarian function, mating behavior, and conception rate in rats given doses up to 20 mg/kg/day (approximately 8 times the recommended human dose on a mg/m^2 basis), however, decreases in mean litter size and fetal body weight, along with delayed ossification were evidenced at greater than or equal to 20 mg/kg/day. In general toxicology studies, changes in the ovary, including hyperplasia, an increase in the incidence of ovarian cysts and a decrease in corpora lutea were observed with variable frequency in mice, rats and dogs at doses that ranged from 3–20 times the human dose on a mg/m^2 basis.

Pregnancy Pregnancy Category D

See WARNINGS.

Nursing Mothers

AROMASIN is only indicated in postmenopausal women. However, radioactivity related to exemestane appeared in rat milk within 15 minutes of oral administration of radiolabeled exemestane. Concentrations of exemestane and its metabolites were approximately equivalent in the milk and plasma of rats for 24 hours after a single oral dose of 1 mg/kg ^14C-exemestane. It is not known whether exemestane is excreted in human milk. Because many drugs are excreted in human milk, caution should be exercised if a nursing woman is inadvertently exposed to AROMASIN (see WARNINGS).

Pediatric Use

The safety and effectiveness of AROMASIN in pediatric patients have not been evaluated.

Geriatric Use

The use of AROMASIN in geriatric patients does not require special precautions.

ADVERSE REACTIONS

Adjuvant Treatment of Early Breast Cancer

AROMASIN tolerability in postmenopausal women with early breast cancer was evaluated in two well-controlled trials: the IES study (see CLINICAL STUDIES) and the 027 study (a randomized, placebo-controlled, double-blind, parallel group study specifically designed to assess the effects of exemestane on bone metabolism, hormones, lipids and coagulation factors over 2 years of treatment).

Certain adverse events, expected based on the known pharmacological properties and side effect profiles of test drugs, were actively sought through a positive checklist. Signs and symptoms were graded for severity using CTC in both studies. Within the IES study, the presence of some illnesses/conditions was monitored through a positive checklist without assessment of severity. These included myocardial infarction, other cardiovascular disorders, gynecological disorders, osteoporosis, osteoporotic fractures, other primary cancer, and hospitalizations.

The median duration of adjuvant treatment was 27.4 months and 27.3 months for patients receiving AROMASIN or tamoxifen, respectively, within the IES study and 23.9 months for patients receiving AROMASIN or placebo within the 027 study. Median duration of observation after randomization for AROMASIN was 34.5 months and for tamoxifen was 34.6 months. Median duration of observation was 30 months for both groups in the 027 study.

AROMASIN was generally well tolerated and adverse events were usually mild to moderate. Within the IES study discontinuations due to adverse events occurred in 6.3% and 5.1% of patients receiving AROMASIN and tamoxifen, respectively, and in 12.3% and 4.1% of patients receiving exemestane or placebo within study 027. Deaths due to any cause were reported for 1.3% of the exemestane-treated patients and 1.4% of the tamoxifen-treated patients within the IES study. There were 6 deaths due to stroke on the exemestane arm compared to 2 on tamoxifen. There were 5 deaths due to cardiac failure on the exemestane arm compared to 2 on tamoxifen.

The incidence of cardiac ischemic events (myocardial infarction, angina and myocardial ischemia) was 1.6% in exemestane treated patients and 0.6% in tamoxifen treated patients in the IES study. Cardiac failure was observed in 0.4% of exemestane treated patients and 0.3% of tamoxifen treated patients.

Treatment-emergent adverse events and illnesses including all causalities and occurring with an incidence of ≥5% in either treatment group of the IES study during or within one month of the end of treatment are shown in Table 8.

Table 8. Incidence (%) of Adverse Events of all Grades* and Illnesses Occurring in (≥5%) of Patients in Any Treatment Group in Study IES in Postmenopausal Women with Early Breast Cancer
 |  | % of patients
Body system and Adverse Event by MedDRA dictionary | AROMASIN 25 mg daily (N=2252) |  | Tamoxifen 20 mg daily† (N=2280)
Eye Visual disturbances‡ | 5.0 |  | 3.8
Gastrointestinal Nausea‡ | 8.5 |  | 8.7
General Disorders Fatigue‡ | 16.1 |  | 14.7
Musculoskeletal Arthralgia Pain in limb Back pain Osteoarthritis | 14.6 9.0 8.6 5.9 |  | 8.6 6.4 7.2 4.5
Nervous System Headache‡ Dizziness‡ | 13.1 9.7 |  | 10.8 8.4
Psychiatric Insomnia‡ Depression | 12.4 6.2 |  | 8.9 5.6
Skin & Subcutaneous Tissue Increased sweating‡ | 11.8 |  | 10.4
Vascular Hot flushes‡ Hypertension | 21.2 9.8 |  | 19.9 8.4

* Graded according to Common Toxicity Creiteria;
† 75 patients received tamoxifen 30 mg daily;
‡ Event actively sought.

In the IES study, as compared to tamoxifen, AROMASIN was associated with a higher incidence of events in the musculoskeletal disorders and in the nervous system disorders, including the following events occurring with frequency lower than 5% (osteoporosis [4.6% vs. 2.8%], osteochondrosis and trigger finger [0.3% vs 0 for both events], paresthesia [2.6% vs. 0.9%], carpal tunnel syndrome [2.4% vs. 0.2%], and neuropathy [0.6% vs. 0.1%]. Diarrhea was also more frequent in the exemestane group (4.2% vs. 2.2%). Clinical fractures were reported in 94 patients receiving exemestane (4.2%) and 71 patients receiving tamoxifen (3.1%). After a median duration of therapy of about 30 months and a median follow-up of about 52 months, gastric ulcer was observed at a slightly higher frequency in the AROMASIN group compared to tamoxifen (0.7% versus less than 0.1%). The majority of patients on AROMASIN with gastric ulcer received concomitant treatment with non-steroidal anti-inflammatory agents and/or had a prior history.

Tamoxifen was associated with a higher incidence of muscle cramps [3.1% vs. 1.5%], thromboembolism [2.0% vs. 0.9%], endometrial hyperplasia [1.7% vs. 0.6%], and uterine polyps [2.4% vs. 0.4%].

Common adverse events occurring on study 027 are described in Table 9.

Table 9: Incidence of Selected Treatment-Emergent Adverse Events of all CTC Grades* Occurring in ≥ 5% of Patients in Either Arm on Study 027
Adverse Event | Exemestane N=73 (% incidence) | Placebo N=73 (% incidence)
Hot flushes | 32.9 | 24.7
Arthralgia | 28.8 | 28.8
Increased Sweating | 17.8 | 20.6
Alopecia | 15.1 | 4.1
Hypertension | 15.1 | 6.9
Insomnia | 13.7 | 15.1
nausea | 12.3 | 16.4
Fatigue | 11.0 | 19.2
Abdominal pain | 11.0 | 13.7
Depression | 9.6 | 6.9
Diarrhea | 9.6 | 1.4
Dizziness | 9.6 | 9.6
Dermatitis | 8.2 | 1.4
Headache | 6.9 | 4.1
Myalgia | 5.5 | 4.1
Edema | 5.5 | 6.9
Anxiety | 4.1 | 5.5

* Most events were CTC grade 1-2
Treatment of Advanced Breast Cancer

A total of 1058 patients were treated with exemestane 25 mg once daily in the clinical trials program. Exemestane was generally well tolerated, and adverse events were usually mild to moderate. Only one death was considered possibly related to treatment with exemestane; an 80-year-old woman with known coronary artery disease had a myocardial infarction with multiple organ failure after 9 weeks on study treatment. In the clinical trials program, only 3% of the patients discontinued treatment with exemestane because of adverse events, mainly within the first 10 weeks of treatment; late discontinuations because of adverse events were uncommon (0.3%).

In the comparative study, adverse reactions were assessed for 358 patients treated with AROMASIN and 400 patients treated with megestrol acetate. Fewer patients receiving AROMASIN discontinued treatment because of adverse events than those treated with megestrol acetate (2% vs. 5%). Adverse events that were considered drug related or of indeterminate cause included hot flashes (13% vs. 5%), nausea (9% vs. 5%), fatigue (8% vs. 10%), increased sweating (4% vs. 8%), and increased appetite (3% vs. 6%). The proportion of patients experiencing an excessive weight gain (greater than 10% of their baseline weight) was significantly higher with megestrol acetate than with AROMASIN (17% vs. 8%). Table 10 shows the adverse events of all CTC grades, regardless of causality, reported in 5% or greater of patients in the study treated either with AROMASIN or megestrol acetate.

Table 10. Incidence (%) of Adverse Events of all Grades* and Causes Occurring in ≥5% of Advanced Breast Cancer Patients In Each Treatment Arm in the Comparative Study
Body system and Adverse Event by WHO ART dictionary | AROMASIN 25 mg once daily (N=358) | Megestrol Acetate 40 mg QID (N=400)
Autonomic Nervous Increased sweating | 6 | 9
Body as a Whole Fatigue Hot flashes Pain Influenza-like symptoms Edema (includes edema, peripheral edema, leg edema) | 22 13 13 6 7 | 29 6 13 5 6
Cardiovascular Hypertension | 5 | 6
Nervous Depression Insomnia Anxiety Dizziness Headache | 13 11 10 8 8 | 9 9 11 6 7
Gastrointestinal Nausea Vomiting Abdominal pain Anorexia Constipation Diarrhea Increased appetit | 18 7 6 6 5 4 3 | 12 4 11 5 8 5 6
Respiratory Dyspnea Coughing | 10 6 | 15 7

* Graded according to Common Toxicity Criteria

Less frequent adverse events of any cause (from 2% to 5%) reported in the comparative study for patients receiving AROMASIN 25 mg once daily were fever, generalized weakness, paresthesia, pathological fracture, bronchitis, sinusitis, rash, itching, urinary tract infection, and lymphedema.

Additional adverse events of any cause observed in the overall clinical trials program (N = 1058) in 5% or greater of patients treated with exemestane 25 mg once daily but not in the comparative study included pain at tumor sites (8%), asthenia (6%) and fever (5%). Adverse events of any cause reported in 2% to 5% of all patients treated with exemestane 25 mg in the overall clinical trials program but not in the comparative study included chest pain, hypoesthesia, confusion, dyspepsia, arthralgia, back pain, skeletal pain, infection, upper respiratory tract infection, pharyngitis, rhinitis, and alopecia.

Post-marketing Experience

The following adverse reactions have been identified during post approval use of Aromasin. Because reactions are reported voluntarily from a population of uncertain size, it is not always possible to reliably estimate their frequency or establish a causal relationship to drug exposure.

Cases of hepatitis including cholestatic hepatitis have been observed in clinical trials and reported through post-marketing surveillance.

OVERDOSAGE

Clinical trials have been conducted with exemestane given as a single dose to healthy female volunteers at doses as high as 800 mg and daily for 12 weeks to postmenopausal women with advanced breast cancer at doses as high as 600 mg. These dosages were well tolerated. There is no specific antidote to overdosage and treatment must be symptomatic. General supportive care, including frequent monitoring of vital signs and close observation of the patient, is indicated.

A male child (age unknown) accidentally ingested a 25-mg tablet of exemestane. The initial physical examination was normal, but blood tests performed 1 hour after ingestion indicated leucocytosis (WBC 25000/mm^3 with 90% neutrophils). Blood tests were repeated 4 days after the incident and were normal. No treatment was given.

In mice, mortality was observed after a single oral dose of exemestane of 3200 mg/kg, the lowest dose tested (about 640 times the recommended human dose on a mg/m^2 basis). In rats and dogs, mortality was observed after single oral doses of exemestane of 5000 mg/kg (about 2000 times the recommended human dose on a mg/m^2 basis) and of 3000 mg/kg (about 4000 times the recommended human dose on a mg/m^2 basis), respectively.

Convulsions were observed after single doses of exemestane of 400 mg/kg and 3000 mg/kg in mice and dogs (approximately 80 and 4000 times the recommended human dose on a mg/m^2 basis), respectively.

DOSAGE AND ADMINISTRATION

The recommended dose of AROMASIN in early and advanced breast cancer is one 25 mg tablet once daily after a meal.

In postmenopausal women with early breast cancer who have been treated with 2–3 years of tamoxifen, treatment with AROMASIN should continue in the absence of recurrence or contralateral breast cancer until completion of five years of adjuvant endocrine therapy.

For patients with advanced breast cancer, treatment with AROMASIN should continue until tumor progression is evident.

For patients receiving AROMASIN with a potent CYP 3A4 inducer such as rifampicin or phenytoin, the recommended dose of AROMASIN is 50 mg once daily after a meal.

The safety of chronic dosing in patients with moderate or severe hepatic or renal impairment has not been studied. Based on experience with exemestane at repeated doses up to 200 mg daily that demonstrated a moderate increase in non-life threatening adverse events, dosage adjustment does not appear to be necessary (see CLINICAL PHARMACOLOGY, Special Populations and PRECAUTIONS).

HOW SUPPLIED

AROMASIN Tablets are round, biconvex, and off-white to slightly gray. Each tablet contains 25 mg of exemestane. The tablets are printed on one side with the number "7663" in black. AROMASIN is packaged in HDPE bottles with a child-resistant screw cap, supplied in packs of 30 tablets.

30-tablet HDPE bottle NDC 54868-5261-0

Store at 25°C (77°F); excursions permitted to 15°–30°C (59°–86°F) [see USP Controlled Room Temperature].

Rx only

Distributed by

Pfizer Pharmacia & Upjohn Company

Division of Pfizer Inc., NY, NY 10017

PRINCIPAL DISPLAY PANEL

AROMASIN Tablets